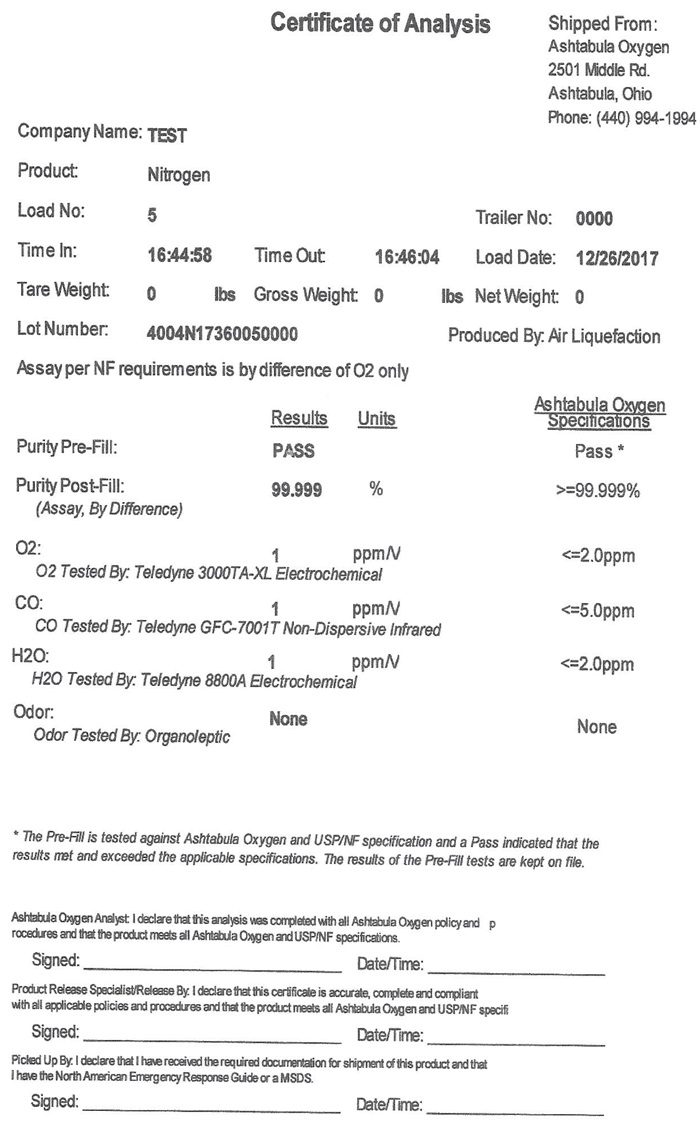 DRUG LABEL: Nitrogen
NDC: 71408-003 | Form: GAS
Manufacturer: Ineos Pigments ASU LLC
Category: prescription | Type: HUMAN PRESCRIPTION DRUG LABEL
Date: 20241027

ACTIVE INGREDIENTS: NITROGEN 99 L/100 L

Nitrogen

Certificate of Analysis Shipped From:

Ashtabula Oxygen

2501 Middle Rd.

Ashtabula, Ohio

Phone: (440) 994-1994

Company Name: TEST

Product: Nitrogen

Load No: 5 Trailer No: 0000

Time In: 16:44:58 Time Out: 16:46:04 Load Date: 12/26/2017

Tare Weight: 0 Gross Weight: 0 lbs Net Weight: 0 lbs

Lot Number: 4004N17360050000 Produced by: Air Liquefaction

Assay per NF requirements is by difference of O2 only

Ashtabula Oxygen

Results Units Specifications

Purity Pre-Fill: PASS Pass*

Purity Post-Fill: 99.99 % >=99.999%

Assay, By Difference)

O2: ppm/V <=2.0ppm

O2 Tested By: Teledyne 3000TA-XL Electrochemcial

CO: ppm/V <=5.0ppm

CO Tested By: Teledyne GFC-7001T Non-Dispersive Infrared

H2O: ppm/V <=2.0ppm

H20 Tested By: Teledyne 8800A Electrochemcial

Odor: None None

Odor Tested By: Organoleptic

- The Pre-Fill is tested against Ashtabula Oxygen and USP/NF specification and a “Pass” indicated that the results met and exceeded the applicable specifications. The results of the Pre-Fill tests are kept on file.

Ashtabula Oxygen Analyst: I declare that this analysis was completed with all Ashtabula Oxygen policy and procedures and that the product meets all Ashtabula Oxygen and USP/NF specifications.

Signed: Date/Time:

Product Release Specialist/Release By: I declare that this certification is accurate, complete and compliant with all applicable policies and procedures and that the product meets all Ashtabula Oxygen and USP/NF specifications.

Signed: Date/Time:

Picked Up By: I declare that I have received the required documentation for shipment of this product and that I have the North American Emergency Response Guide or a MSDS.

Signed: Date/Time: